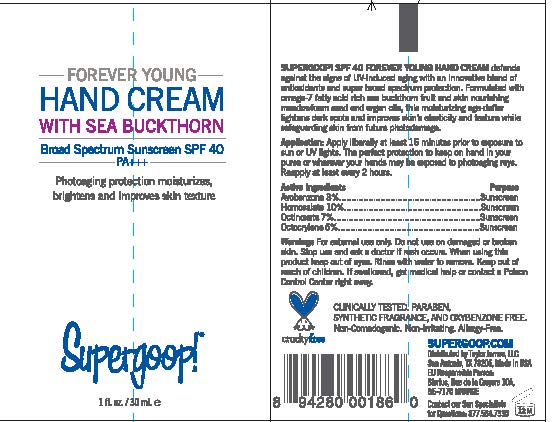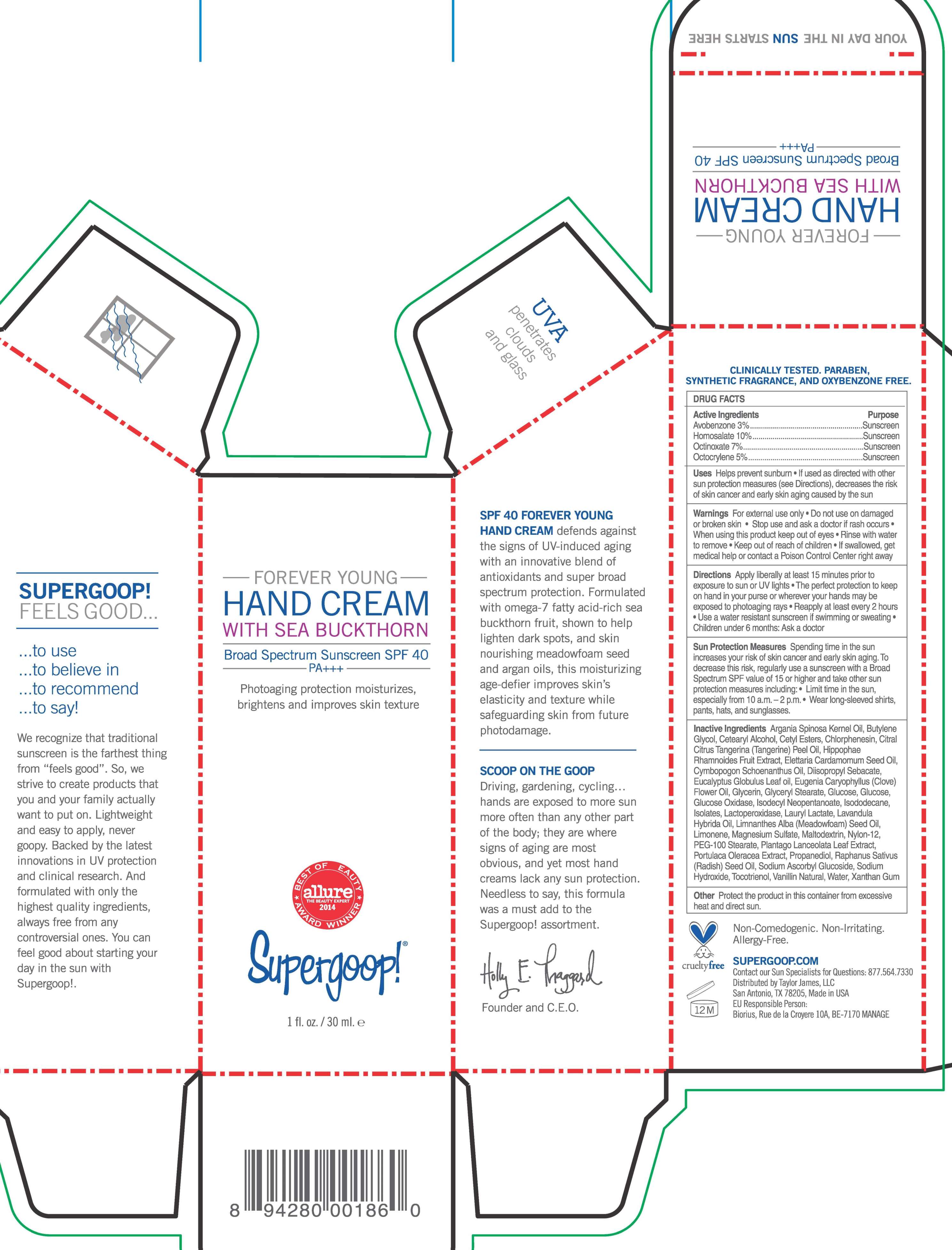 DRUG LABEL: Forever Young Hand Broad Spectrum SPF 40

NDC: 75936-128 | Form: CREAM
Manufacturer: TAYLOR JAMES, LTD.
Category: otc | Type: HUMAN OTC DRUG LABEL
Date: 20201112

ACTIVE INGREDIENTS: AVOBENZONE 3 g/100 mL; HOMOSALATE 10 g/100 mL; OCTINOXATE 7 g/100 mL; OCTOCRYLENE 5 g/100 mL
INACTIVE INGREDIENTS: ARGAN OIL; MEDIUM-CHAIN TRIGLYCERIDES; CETOSTEARYL ALCOHOL; CETYL ESTERS WAX; CHLORPHENESIN; CITRAL; MANDARIN OIL; CYMBOPOGON SCHOENANTHUS OIL; DIISOPROPYL SEBACATE; CARDAMOM OIL; EUCALYPTUS OIL; CLOVE OIL; GLYCERIN; GLYCERYL MONOSTEARATE; DEXTROSE; GLUCOSE OXIDASE; ISODECYL NEOPENTANOATE; ISODODECANE; LACTOPEROXIDASE BOVINE; LAURYL LACTATE; LAVANDIN OIL; MEADOWFOAM SEED OIL; LIMONENE, (+)-; MAGNESIUM SULFATE, UNSPECIFIED FORM; NYLON-12; PEG-100 STEARATE; PLANTAGO LANCEOLATA LEAF; PROPANEDIOL; SODIUM HYDROXIDE; WATER; XANTHAN GUM

Forever Young Hand Cream Broad Spectrum SPF 40

Active Ingredients Purpose

Avobenzone 3% Sunscreen

Homosalate 10% Sunscreen

Octinoxate 7% Sunscreen

Octocrylene 5% Sunscreen

PURPOSE

Helps prevent Sunburn -If used as directed with other sun protection measures (see Directions), decreases the risk of skin cancer and early skin aging caused by the sun

Keep out of reach of children

Stop use and ask a doctor if rash occurs

Warnings

For External Use only

Do not use on damaged or broken Skin

When using this product keep out of eyes

Rinse with water to remove

If swallowed, get medical help or contact a poison control center right away

DOSAGE AND ADMINISTRATION

Directions Apply liberally at least 15 minutes prior to exposure to sun or UV lights

The perfect protection to keep in your purse or wherever your hands may be exposed to photoaging rays

Reapply at least every 2 hours

Use a water-resistant sunscreen if swimming or sweating

Children under 6 months Ask a doctor

Sun Protection Measures Spending time in the sun increases your risk of skin cancer and early skin aging. To decrease this risk, regularly use a sunscreen with a Broad Spectrum SPF value of 15 or higher and take other sun protection measures including:

Limit time in the sun, especially from 10 a.m.- 2 p.m.

Wear long-sleeved shirts, pants, hats, and sunglasses

INACTIVE INGREDIENT

Argania Spinosa Kernel Oil, Caprylic/Capric Triglyceride, Cetearyl Alcohol, Cetyl Esters Chlorphenesin, Citral, Citrus Tangerina (Tangerine) Peel Oil, Cymbopogon Schoenanthus Oil, Diisopropyl Sebacate, Elettraria Cardamamomum Seed Oil, Eucalyptus Globulus Leaf Oil, Eugenia Caryophyllus (Clove) Flower Oil, Glycerin, Glyceryl Stearate, Glucose, Glucose Oxidase, Isodecyl Neopenatoate, Isododecane, Isolates, Lactoperoxidase, Lauryl Lactate, Lavandula Hybrida Oil, Limnanthes Alba (Meadowfoam) Seed Oil, Limonene, Magnesium Sulfate, Nylon-12, PEG-100 Stearate, Plantago Lanceolata Leaf Extract, Propanediol, Raphanus Sativus (Radish) Seed Oil, Sodium Hydroxide, Vanillin Natural, Water, Xanthan Gum.

PACKAGE LABEL

Forever young Hand Cream

With Sea Buckthorn

Broad Spectrum Sunscreen SPF 40 PA+++

Supergoop

1 fl. oz./30 mL